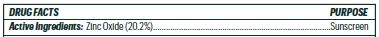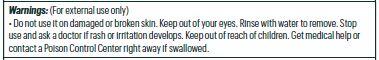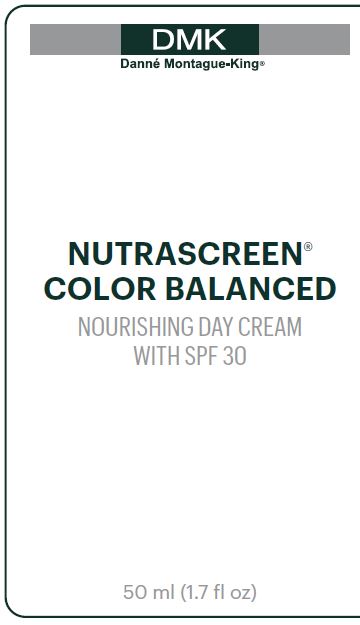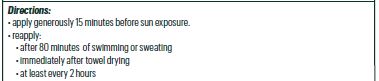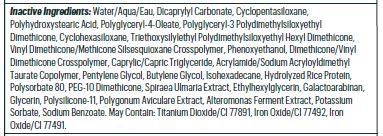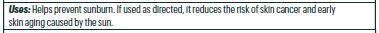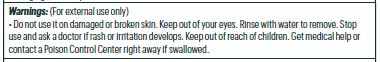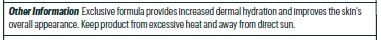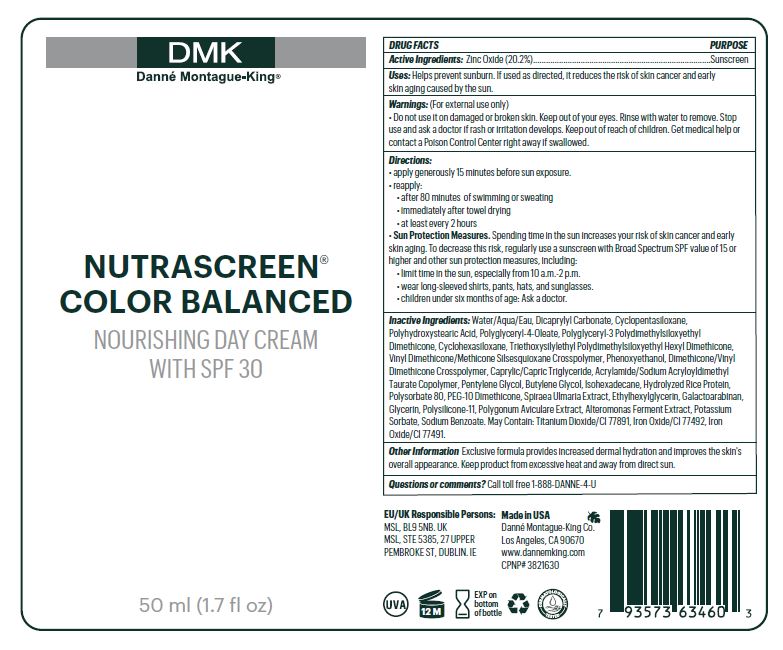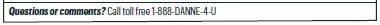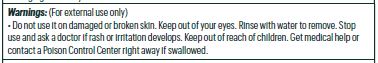 DRUG LABEL: Nutrascreen Color Balanced
NDC: 81537-104 | Form: LOTION
Manufacturer: DMK - Danne Montague King
Category: otc | Type: HUMAN OTC DRUG LABEL
Date: 20240719

ACTIVE INGREDIENTS: ZINC OXIDE 20.24 g/100 mL
INACTIVE INGREDIENTS: CYCLOMETHICONE 5 5.56 g/100 mL; SODIUM ACRYLOYLDIMETHYLTAURATE-ACRYLAMIDE COPOLYMER (1:1; 90000-150000 MPA.S) 0.78 g/100 mL; DIMETHICONE/VINYL DIMETHICONE CROSSPOLYMER (SOFT PARTICLE) 0.05 g/100 mL; FERRIC OXIDE YELLOW 0.4875 g/100 mL; FILIPENDULA ULMARIA FLOWER 0.19 g/100 mL; POLYGONUM AVICULARE WHOLE 0.01 g/100 mL; POLYGLYCERYL-4 OLEATE 3.75 g/100 mL; CYCLOMETHICONE 6 2 g/100 mL; ALTEROMONAS MACLEODII POLYSACCHARIDES 0.0025 g/100 mL; FERRIC OXIDE RED 0.1463 g/100 mL; PEG-10 DIMETHICONE (600 CST) 0.325 g/100 mL; POTASSIUM SORBATE 0.002 g/100 mL; POLYGLYCERYL-3 POLYDIMETHYLSILOXYETHYL DIMETHICONE (4000 MPA.S) 2.3 g/100 mL; VINYL DIMETHICONE/METHICONE SILSESQUIOXANE CROSSPOLYMER 1.3 g/100 mL; WATER 37.8875 g/100 mL; MEDIUM-CHAIN TRIGLYCERIDES 0.975 g/100 mL; SODIUM BENZOATE 0.002 g/100 mL; DICAPRYLYL CARBONATE 9 g/100 mL; POLYHYDROXYSTEARIC ACID (2300 MW) 4 g/100 mL; TRIETHOXYSILYLETHYL POLYDIMETHYLSILOXYETHYL HEXYL DIMETHICONE 1.9 g/100 mL; PHENOXYETHANOL 1.125 g/100 mL; PENTYLENE GLYCOL 0.75 g/100 mL; BUTYLENE GLYCOL 0.67 g/100 mL; ISOHEXADECANE 0.65 g/100 mL; POLYSORBATE 80 0.52 g/100 mL; ETHYLHEXYLGLYCERIN 0.125 g/100 mL; GALACTOARABINAN 0.1037 g/100 mL; GLYCERIN 0.111 g/100 mL; TITANIUM DIOXIDE 3.4125 g/100 mL

Nutrascreen Color Balanced SPF 30